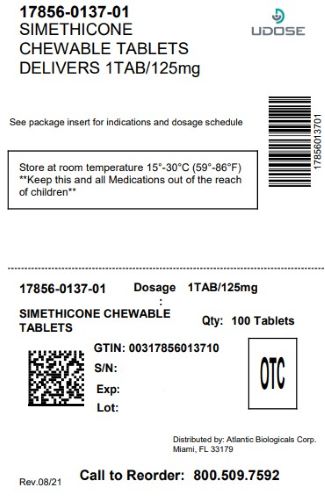 DRUG LABEL: Simethicone 125 mg
NDC: 17856-0137 | Form: TABLET, CHEWABLE
Manufacturer: ATLANTIC BIOLOGICALS CORP.
Category: otc | Type: HUMAN OTC DRUG LABEL
Date: 20250627

ACTIVE INGREDIENTS: DIMETHICONE 125 mg/1 1
INACTIVE INGREDIENTS: SUCROSE; MALTODEXTRIN; PEPPERMINT; SORBITOL; STEARIC ACID; DEXTROSE; CELLULOSE, MICROCRYSTALLINE; SILICON DIOXIDE

Simethicone 125 mg

Drug Facts

Active ingredient (in each chewable tablet)

Simethicone 125 mg

PURPOSE

Antiflatulent

Use

relieves bloating, pressure and fullness commonly referred to as gas

Warnings

Keep out of reach of children

TAMPER EVIDENT: DO NOT USE IF SAFETY POUCH LOOKS TO BE TEMPERED OR OPEN

Keep out of reach of children

Directions

- thoroughly chew 1-2 tablets as needed after meals and at bedtime
- do not take more than 4 tablets per day

Other information

store at room temperature 15°-30°C (59°-86°F)

Inactive ingredients

compressible sugar, dextrose, maltodextrin, microcrystaline cellulose, peppermint flavor, silicon dioxide, sorbitol, stearic acid

How Supplied

NDC 17856-0137-01

Box of 100 Chewable Tablets.................................. 17856-0137-01

ANTIFLATULENT

Questions or comments?

Distributed by:

ATLANTIC BIOLOGICALS CORP.

MIAMI, FL 33179

Call 1-800-509-7592

M-F 8 am - 5 pm EST